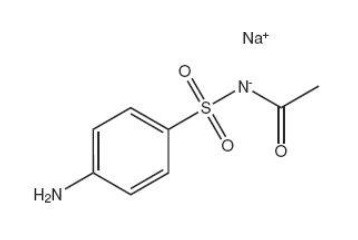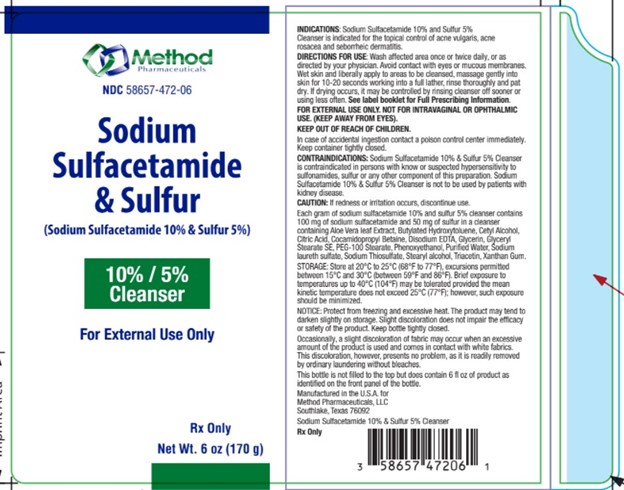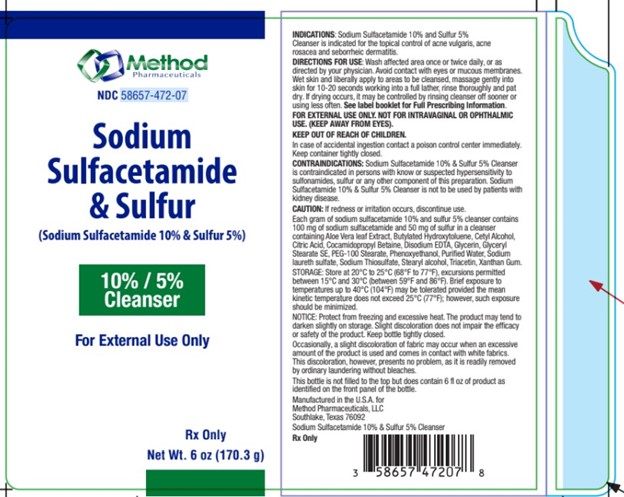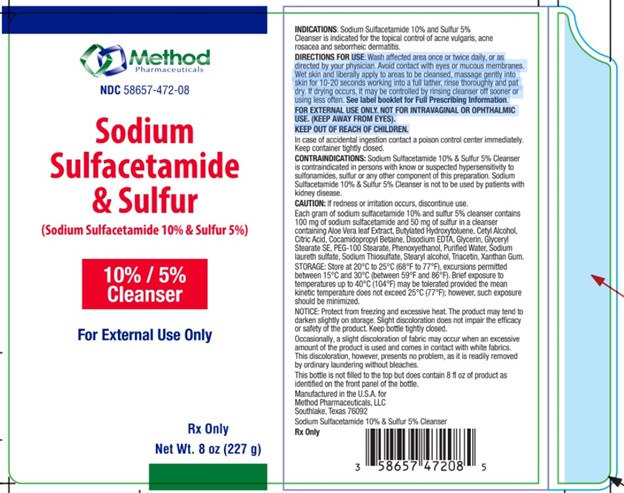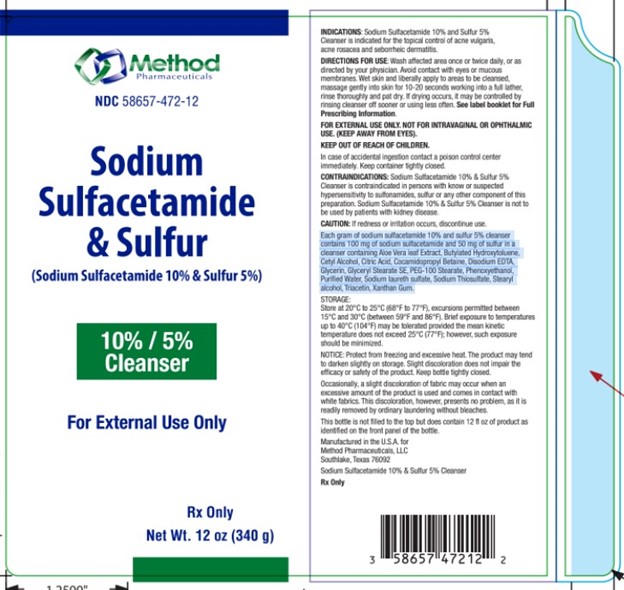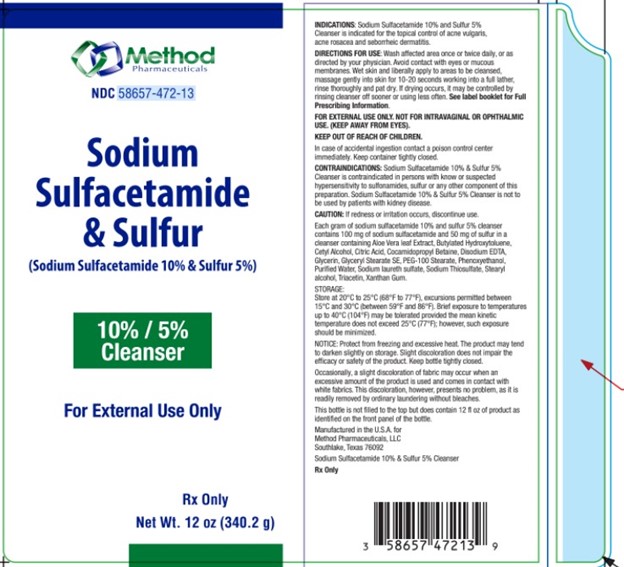 DRUG LABEL: Sodium Sulfacetamide and Sulfur
NDC: 58657-472 | Form: LIQUID
Manufacturer: Method Pharmaceuticals, LLC
Category: prescription | Type: HUMAN PRESCRIPTION DRUG LABEL
Date: 20260212

ACTIVE INGREDIENTS: SULFACETAMIDE SODIUM 100 mg/1 g; SULFUR 50 mg/1 g
INACTIVE INGREDIENTS: BUTYLATED HYDROXYTOLUENE; ALOE VERA LEAF; 1-ETHYL CITRATE; CETYL ALCOHOL; EDETATE DISODIUM; GLYCERYL STEARATE SE; PEG-100 STEARATE; COCAMIDOPROPYL BETAINE; TRIACETIN; WATER; SODIUM THIOSULFATE; SODIUM LAURYL SULFATE; STEARYL ALCOHOL; XANTHAN GUM; GLYCERIN; PHENOXYETHANOL

Sodium Sulfacetamide 10% - Sulfur 5% Cleanser

Rx Only

DESCRIPTION

Each gram of sodium sulfacetamide 10% and sulfur 5% cleanser contains
100 mg of sodium sulfacetamide and 50 mg of sulfur in a cleanser
containing Aloe Vera leaf Extract, Butylated Hydroxytoluene, Cetyl Alcohol,
Citric Acid, Cocamidopropyl Betaine, Disodium EDTA, Glycerin, Glyceryl
Stearate SE, PEG-100 Stearate, Phenoxyethanol, Purified Water, Sodium
laureth sulfate, Sodium Thiosulfate, Stearyl alcohol, Triacetin, Xanthan Gum.
Sodium sulfacetamide is a sulfonamide with antibacterial activity while sulfur acts as a keratolytic agent. Sodium sulfacetamide is C8H9N2NaO 3S·H2O with molecular weight of 254.24. Chemically, it is N-[(4-aminophenyl)sulfonyl]-acetamide, monosodium salt, monohydrate.

The structural formula is:

CLINICAL PHARMACOLOGY

The most widely accepted mechanism of action of sulfonamides is the Woods-Fildes theory, which is based on the fact that sulfonamides act as competitive antagonists to para-aminobenzoic acid (PABA), an essential component for bacterial growth. While absorption through intact skin has not been determined, sodium sulfacetamide is readily absorbed from the gastrointestinal tract when taken orally and excreted in the urine, largely unchanged. The biological half-life has variously been reported as 7 to 12.8 hours.
The exact mode of action of sulfur in the treatment of acne is unknown, but it has been reported that it inhibits the growth of Propionibacterium acnes and the formation of free fatty acids.

INDICATIONS

SODIUM SULFACETAMIDE 10% - SULFUR 5% CLEANSER is indicated for use in the topical control of acne vulgaris, acne rosacea and seborrheic dermatitis.

CONTRAINDICATIONS:

Sodium Sulfacetamide 10% & Sulfur 5% Cleanser is contraindicated in persons with know or suspected hypersensitivity to
sulfonamides, sulfur or any other component of this preparation. Sodium
Sulfacetamide 10% & Sulfur 5% Cleanser is not to be used by patients with
kidney disease.

WARNINGS

Although rare, sensitivity to sodium sulfacetamide may occur. Therefore, caution and careful supervision should be observed when prescribing this drug for patients who may be prone to hypersensitivity to topical sulfonamides. Systemic toxic reactions such as agranulocytosis, acute hemolytic anemia, purpura hemorrhagica, drug fever, jaundice and contact dermatitis indicate hypersensitivity to sulfonamides. Particular caution should be employed if areas of denuded or abraded skin are involved.
Sulfonamides are known to cause Stevens-Johnson syndrome in hypersensitive individuals. Stevens-Johnson syndrome also has been reported following the use of sodium sulfacetamide topically. Cases of drug induced systemic lupus erythematosus from topical sulfacetamide also have been reported. In one of these cases, there was a fatal outcome. KEEP OUT OF REACH OF CHILDREN.

OTHER SAFETY INFORMATION

NOTICE: Protect from freezing and excessive heat. The product may tend to
darken slightly on storage. Slight discoloration does not impair the efficacy
or safety of the product. Keep bottle tightly closed.

Occasionally, a slight discoloration of fabric may occur when an excessive
amount of the product is used and comes in contact with white fabrics.
This discoloration, however, presents no problem, as it is readily removed
by ordinary laundering without bleaches.

DOSAGE AND ADMINISTRATION

USE: Wash affected area once or twice daily, or as
directed by your physician. Avoid contact with eyes or mucous membranes.
Wet skin and liberally apply to areas to be cleansed, massage gently into
skin for 10-20 seconds working into a full lather, rinse thoroughly and pat
dry. If drying occurs, it may be controlled by rinsing cleanser off sooner or
using less often. See label booklet for Full Prescribing Information.
FOR EXTERNAL USE ONLY. NOT FOR INTRAVAGINAL OR OPHTHALMIC
USE. (KEEP AWAY FROM EYES).
KEEP OUT OF REACH OF CHILDREN.